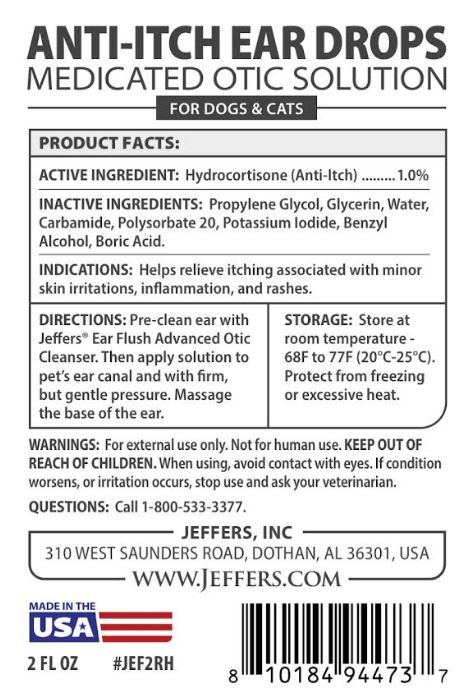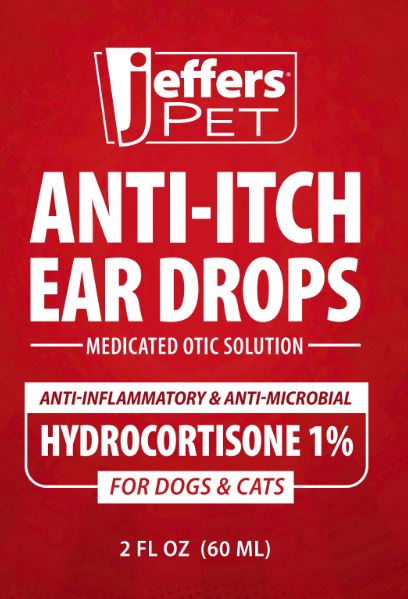 DRUG LABEL: JEFFERS ANTI-ITCH EAR DROPS
NDC: 86010-200 | Form: LIQUID
Manufacturer: JEFFERS
Category: animal | Type: OTC ANIMAL DRUG LABEL
Date: 20250221

ACTIVE INGREDIENTS: HYDROCORTISONE 10 g/1000 g
INACTIVE INGREDIENTS: PROPYLENE GLYCOL; GLYCERIN; WATER; PHENCARBAMIDE; Polysorbate 20; POTASSIUM IODIDE; BENZYL ALCOHOL; BORIC ACID

ANTI-ITCH EAR DROPS - Medicated Otic Solution

Active Ingredient(s):

Hydrocortisone........1% (Anti-Itch)

Indications:

Helps relieve itching associated with minor skin irritations, inflammation, and rashes.

WARNINGS:

For external use only. Not for human use. KEEP OUT OF REACH OF CHILDREN. When using, avoid contact with eyes. If condition worsens, or irritation occurs, stop use and ask your veterinarian.

DIRECTIONS:

Pre-clean ear with Jeffers® Ear Flush Advanced Otic Cleanser. Then apply solution to pet’s ear canal and with firm, but gentle pressure. Massage
the base of the ear.

STORAGE:

Store at room temperature - 68F to 77F (20°C-25°C). Protect from freezing or excessive heat.

INACTIVE INGREDIENTS:

Propylene Glycol, Glycerin, Water, Carbamide, Polysorbate 20, Potassium Iodide, Benzyl Alcohol, Boric Acid.

QUESTIONS:

Call 1-800-533-3377